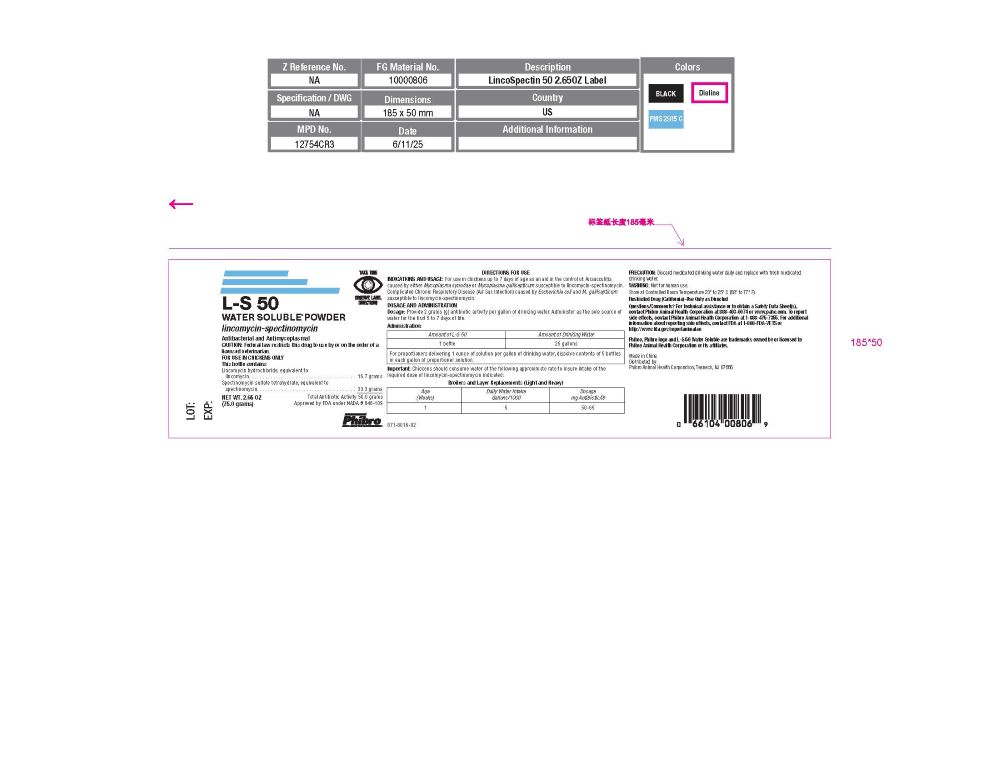 DRUG LABEL: L-S 50
NDC: 66104-1108 | Form: POWDER, FOR SOLUTION
Manufacturer: Phibro Animal Health
Category: animal | Type: PRESCRIPTION ANIMAL DRUG LABEL
Date: 20260122

ACTIVE INGREDIENTS: LINCOMYCIN HYDROCHLORIDE 16.7 g/75 g; SPECTINOMYCIN SULFATE TETRAHYDRATE 33.3 g/75 g

L-S 50
WATER SOLUBLE® POWDER
lincomycin-spectinomycin

L-S 50
WATER SOLUBLE® POWDER
lincomycin-spectinomycin
Antibacterial and Antimycoplasmal
CAUTION: Federal law restricts this drug to use by or on the order of a licensed veterinarian.
FOR USE IN CHICKENS ONLY

This bottle contains:
Lincomycin hydrochloride, equivalent to
lincomycin. . . . . . . . . . . . . . . . . . . . . . . . . . . . . . . . . . . . . . . 16.7 grams
Spectinomycin sulfate tetrahydrate, equivalent to
spectinomycin. . . . . . . . . . . . . . . . . . . . . . . . . . . . . . . . . . . . 33.3 grams
Total Antibiotic Activity 50.0 grams

Approved by FDA under NADA # 046-109

NET WT. 2.65 OZ (75.0 grams)

INDICATIONS AND USAGE

For use in chickens up to 7 days of age as an aid in the control of: Airsacculitis caused by either Mycoplasma synoviae or Mycoplasma gallisepticum susceptible to lincomycin-spectinomycin. Complicated Chronic Respiratory Disease (Air Sac Infection) caused by Escherichia coli and M. gallisepticum susceptible to lincomycin-spectinomycin.

DOSAGE AND ADMINISTRATION

Dosage

Provide 2 grams (g) antibiotic activity per gallon of drinking water. Administer as the sole source of water for the first 5 to 7 days of life.

Administration

Amount of L-S 50 | Amount of Drinking Water
1 bottle | 25 gallons
For proportioners delivering 1 ounce of solution per gallon of drinking water, dissolve contents of 5 bottles in each gallon of proportioner solution.

Important

Important: Chickens should consume water at the following approximate rate to insure intake of the required dose of lincomycin-spectinomycin indicated:

Broilers and Layer Replacements (Light and Heavy)
Age (Weeks) | Daily Water Intake Gallons/1000 | Dosage mg Antibiotic/lb
1 | 5 | 50-65

PRECAUTION

Discard medicated drinking water daily and replace with fresh medicated drinking water.

WARNING

Not for human use.

Storage

Store at Controlled Room Temperature 20° to 25° C (68° to 77° F).

SAFE HANDLING WARNING

Restricted Drug (California)-Use Only as Directed

Questions/Comments? For technical assistance or to obtain a Safety Data Sheet(s), contact Phibro Animal Health Corporation at 888-403-0074 or

www.pahc.com. To report side effects, contact Phibro Animal Health at 1-888-475-7355. For additional information about reporting side effects for
animal drugs, contact FDA at 1-888-FDA-VETS or https://www.fda.gov/reportanimalae

Phibro, Phibro logo and L-S 50 Water Soluble are trademarks owned by or licensed to Phibro Animal Health Corporation or its affiliates.

Made in China
Distributed by:

Phibro Animal Health Corporation
Teaneck, NJ 07666

871-8016-02

PRINCIPAL DISPLAY PANEL - 75 g Bottle Label

L-S 50 Water Label